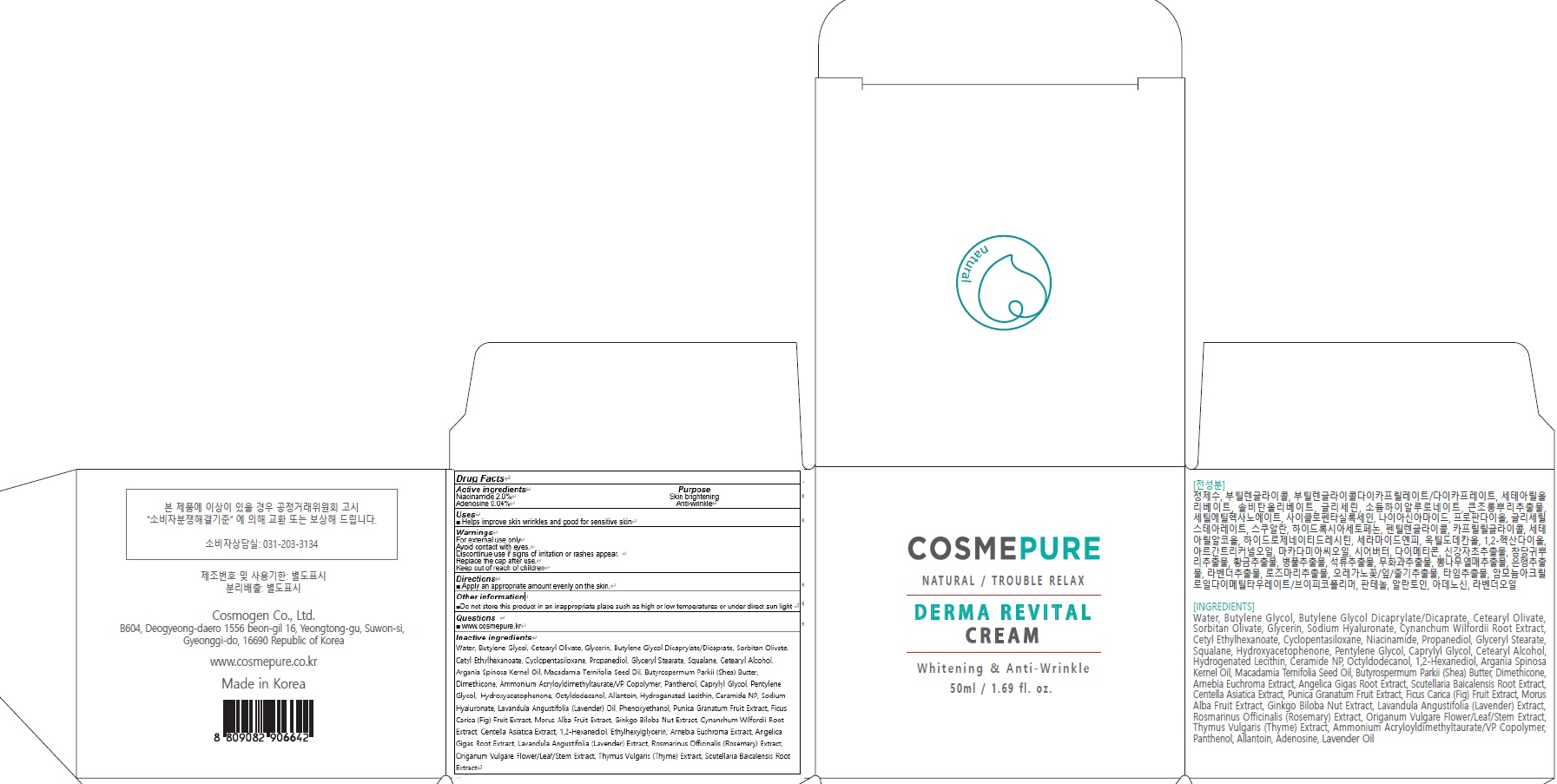 DRUG LABEL: COSMEPURE DERMA REVITAL
NDC: 81418-030 | Form: CREAM
Manufacturer: Cosmogen Co., Ltd.
Category: otc | Type: HUMAN OTC DRUG LABEL
Date: 20210129

ACTIVE INGREDIENTS: Niacinamide 1.0 g/50 mL; Adenosine 0.02 g/50 mL
INACTIVE INGREDIENTS: Water; Butylene Glycol

ACTIVE INGREDIENTS

Niacinamide 2.0%
Adenosine 0.04%

INACTIVE INGREDIENTS

Water, Butylene Glycol, Cetearyl Olivate, Glycerin, Butylene Glycol Dicaprylate/Dicaprate, Sorbitan Olivate, Cetyl Ethylhexanoate, Cyclopentasiloxane, Propanediol, Glyceryl Stearate, Squalane, Cetearyl Alcohol, Argania Spinosa Kernel Oil, Macadamia Ternifolia Seed Oil, Butyrospermum Parkii (Shea) Butter, Dimethicone, Ammonium Acryloyldimethyltaurate/VP Copolymer, Panthenol, Caprylyl Glycol, Pentylene Glycol, Hydroxyacetophenone, Octyldodecanol, Allantoin, Hydrogenated Lecithin, Ceramide NP, Sodium Hyaluronate, Lavandula Angustifolia (Lavender) Oil, Phenoxyethanol, Punica Granatum Fruit Extract, Ficus Carica (Fig) Fruit Extract, Morus Alba Fruit Extract, Ginkgo Biloba Nut Extract, Cynanchum Wilfordii Root Extract, Centella Asiatica Extract, 1,2-Hexanediol, Ethylhexylglycerin, Arnebia Euchroma Extract, Angelica Gigas Root Extract, Lavandula Angustifolia (Lavender) Extract, Rosmarinus Officinalis (Rosemary) Extract, Origanum Vulgare Flower/Leaf/Stem Extract, Thymus Vulgaris (Thyme) Extract, Scutellaria Baicalensis Root Extract

PURPOSE

Skin brightening
Anti wrinkle

WARNINGS

For external use only
Avoid contact with eyes.
Discontinue use if signs of irritation or rashes appear.
Replace the cap after use.
Keep out of reach of children

KEEP OUT OF REACH OF CHILDREN

Uses

■ Helps improve skin wrinkles and good for sensitive skin

Directions

■ Apply an appropriate amount evenly on the skin.

Other information

■ Do not store this product in an inappropriate place such as high or low temperatures or under direct sun light

QUESTIONS

■ www.cosmepure.kr